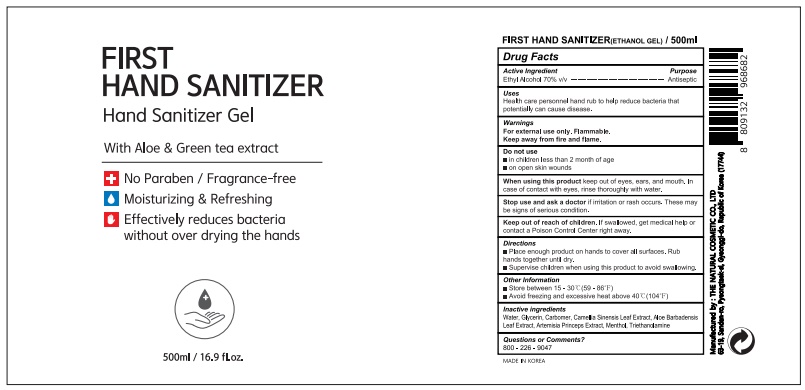 DRUG LABEL: FIRST HAND SANITIZER
NDC: 76764-7777 | Form: GEL
Manufacturer: THE NATURAL COSMETIC CO., LTD
Category: otc | Type: HUMAN OTC DRUG LABEL
Date: 20200625

ACTIVE INGREDIENTS: ALCOHOL 80 mL/100 mL
INACTIVE INGREDIENTS: GLYCERIN; MENTHOL; CARBOMER 940; ALOE VERA LEAF; TROLAMINE; WATER; GREEN TEA LEAF; ARTEMISIA PRINCEPS LEAF

FIRST HAND SANITIZER ETHANOL GEL 500ml

Active Ingredient

Ethyl Alcohol 70% v/v

Purpose

Antiseptic

Use

Health care personnel hand rub to help reduce bacteria that potentially can cause disease.

Warnings

For external use only. Flammable.

Keep away from fire and flame.

Do not use

in children less than 2 month of age

on open skin wounds

When using this product

keep out of eyes, ears, and mouth. In case of contact with eyes, rinse thoroughly with water.

Stop use and ask a doctor

If irritation or rash occurs, These may be signs of serious condition.

Keep out of reach of children

If swallowed, get medical help or contact a Poison Control Center right away.

Directions

Place enough product on hands to cover all surfaces.

Rub hands together until dry.

Supervise children when using this product to avoid swallowing.

Other information

Store between 15 - 30C(59-86F)

Avoid freezing and excessive heat above 40C(104F)

Inactive ingredients

Water, Glycerin, Carbomer, Camellia Sinensis Leaf Extract, Aloe Barbadensis Leaf Extract, Artemisia Princeps Extract, Menthol, Triethanolamine

Questions or Comments?

800-226-9047

Package Label

FIRST

HAND SANITIZER

Hand Sanitizer Gel

With Aloe & Green tea extract

No Paraben / Fragrance-free

Moisturizing & Refreshing

Effectively reduces bacteria

without over drying the hands